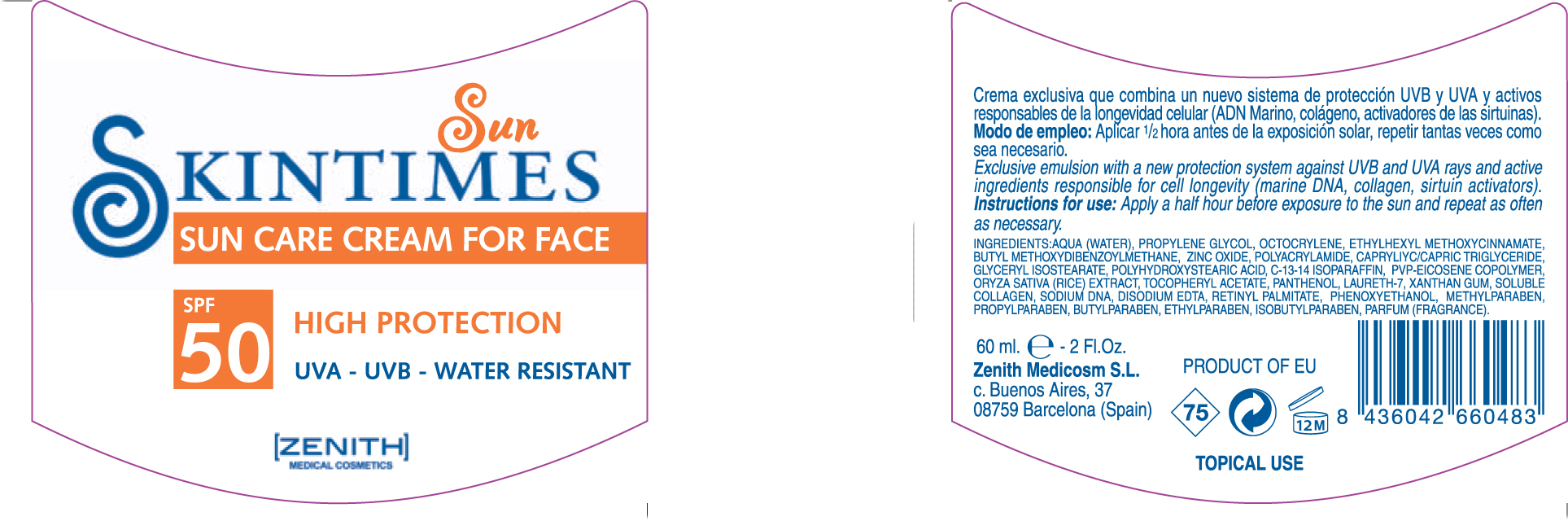 DRUG LABEL: Sun Care
NDC: 42248-120 | Form: CREAM
Manufacturer: Zenith Medicosm SL
Category: otc | Type: HUMAN OTC DRUG LABEL
Date: 20120121

ACTIVE INGREDIENTS: OCTINOXATE 4.5 mL/60 mL; AVOBENZONE  1.8 mL/60 mL; ZINC OXIDE 14.4 mL/60 mL; OCTOCRYLENE 4.5 mL/60 mL
INACTIVE INGREDIENTS: SODIUM DESOXYCHOLATE; PROPYLPARABEN; METHYLPARABEN; COLLAGEN, SOLUBLE, FISH SKIN; PROPYLENE GLYCOL; POLYQUATERNIUM-7 (70/30 ACRYLAMIDE/DADMAC; 900 KD); WATER; TRICAPRYLIN; GLYCERYL ISOSTEARATE; POLYHYDROXYSTEARIC ACID (2300 MW); C12-14 ISOPARAFFIN; 1-ETHYL-2-PYRROLECARBOXALDEHYDE; RICE GERM; ALPHA-TOCOPHEROL ACETATE; PANTHENOL; LAURETH-7; XANTHAN GUM; EDETATE DISODIUM; METHYLPARABEN; ISOBUTYLPARABEN; VITAMIN A PALMITATE; PHENOXYETHANOL; BUTYLPARABEN; ETHYLPARABEN

Drug Facts

Active Ingredient

Octinoxate 7.5%

Octocrylene 10%

Avobenzone 3%

Zinc Oxide 24%

Description

SUN CARE CREAM FOR FACE

SPF 50

HIGH PROTECTION

UVA - UVB - WATER RESISTANT

Exclusive emulsion with a a new protection system against UVA and UVB rays and active ingredients responsible for cell longevity (marine DNA, collagen, sirtuin activators).

60ml. 2Fl.Oz.

Warning

TOPICAL USE

Instructions for use

Apply half hour before exposure to the sun and repeat as often as necessary.